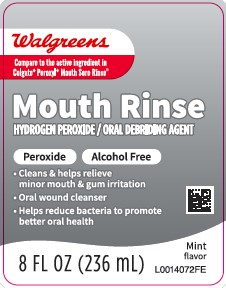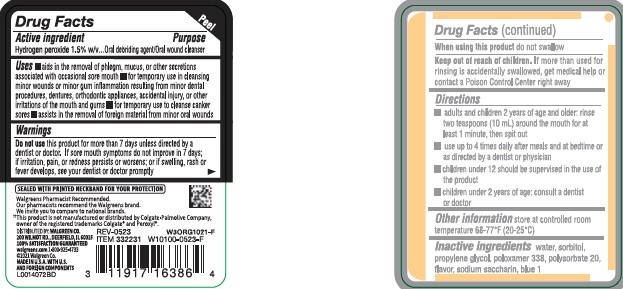 DRUG LABEL: Sore Mouth Cleanser
NDC: 0363-0085 | Form: MOUTHWASH
Manufacturer: Walgreen Co.
Category: otc | Type: HUMAN OTC DRUG LABEL
Date: 20260212

ACTIVE INGREDIENTS: HYDROGEN PEROXIDE 15 mg/1 mL
INACTIVE INGREDIENTS: WATER; SORBITOL; PROPYLENE GLYCOL; POLOXAMER 338; POLYSORBATE 20; FD&C BLUE NO. 1; SACCHARIN SODIUM

Walgreens 462.002/462AA rev 1
Alcohol-Free Mint Peroxide Rinse

Active ingredient

Hydrogen peroxide 1.5% w/v

Purpose

Oral debriding agent/Oral wound cleanser

Uses

- aids in the removal of phlgem, mucus, or other secretions associated with occasional sore mouth
- for temporary use in cleansing minor wounds or minor gum inflammation resulting from minor dental procedures, dentures, orthodontic appliances, accidental injury, or other irritations of the mouth and gums
- for temporary use to cleanse canker sores
- assists in the removal of foreign material from minor oral wounds

Warnings

for this product

Do not use

this product for more than 7 days unless directed by a dentist or doctor. If sore mouth symptoms do not improve in 7 days; if irritation, pain, or redenss persists or worsens; or if swelling, rash or fever develops, see your dentist or doctor promptly

When using this product

do not swallow

Keep out of reach of children.

If more than used for rinsing is accidentally swallowed, get medical help or contact a Poison Control Center right away.

Directions

- adults and children 2 years of age and older: rinse two teaspoons (10 mL) around the mouth for at least 1 minute, then spit out
- use up to 4 times daily after meals and at bedtime or as directed by a dentist or physicial
- children under 12 should be supervised in the use of the product
- children under 2 years of age: consult a dentist or doctor

Other information

store at controlled room temperature 68-77°F (20-25°C)

Inactive ingredients

water, sorbitol, propylene glycol, poloxamer 338, polysorbate 20, flavor, sodium saccharin, blue 1

ADVERSE REACTION

SEALED WITH PRINTED NECKBAND FOR YOUR PROTECTION

Walgreens Pharmacist Recommended

Our Pharmacists recommend the Walgreens brand.

We invite you to compare to national brands.

††This product is not manufactured or distributed by Colgate-Palmolive Company, owner of the registered trademarks Colgate®and Peroxyl®.

DISTRIBUTED BY: WALGREEN CO.

200 WILMOT RD., DEERFIELD, IL 60015

100% SATISFACTION GUARANTEED

walgreens.com 1-800-925-4733

©2021 WALGREEN CO.

MADE IN U.S.A WITH U.S. AND FOREIGN COMPONENTS

Principal Panel Display

Walgreens

Compare to active ingredient in Colgate®Peroxyl®Mouth Sore Rinse††

Mouth Rinse

HYDROGEN PEROXIDE/ORAL DEBRIDING AGENT

Peroxide Alcohol Free

- Cleans & helps relieve minor mouth & gum irritation
- Oral wound cleanser
- Helps reduce bacteria to promte better oral health

8 FL OZ (236 mL)

Mint Flavor